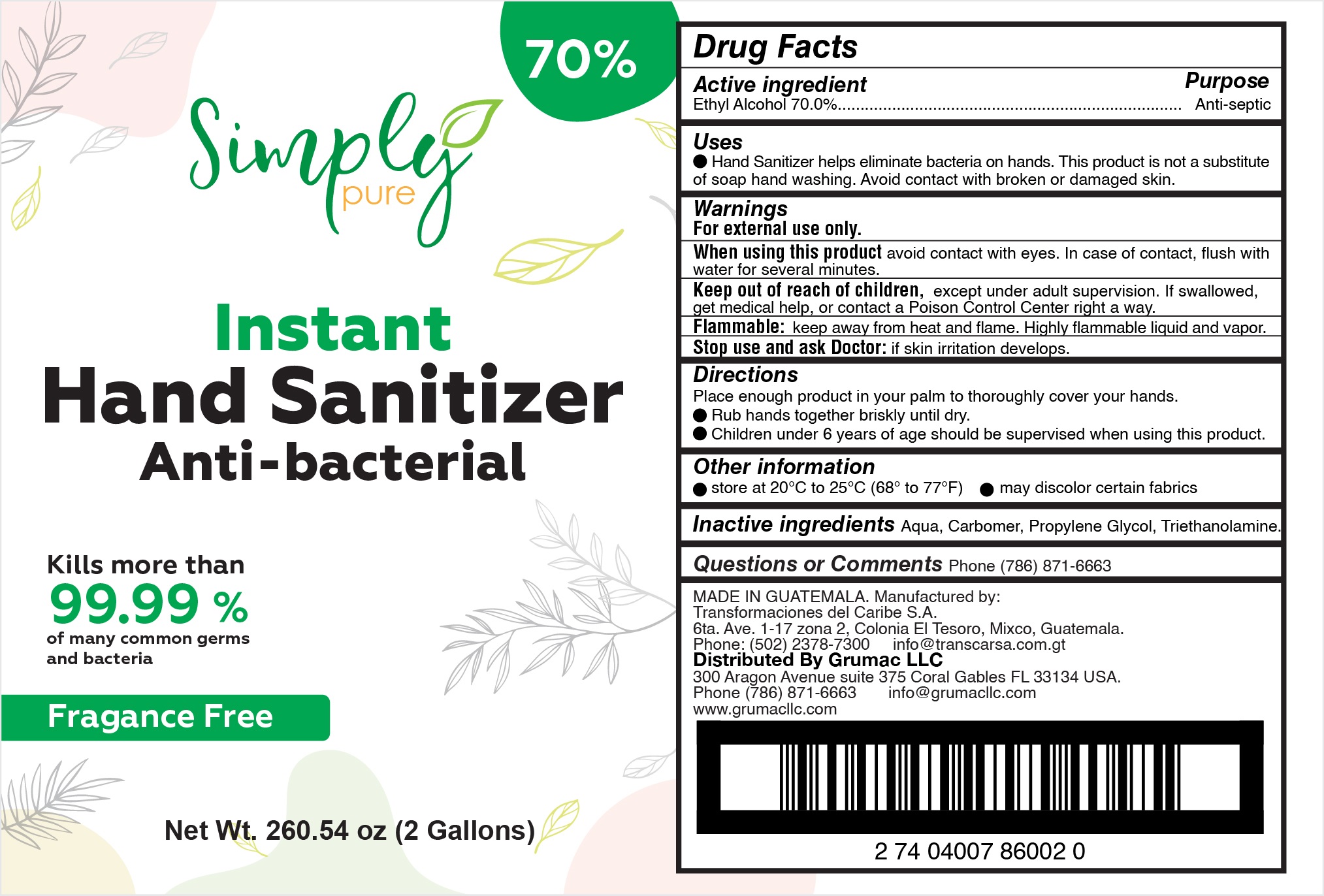 DRUG LABEL: Hand Sanitizer
NDC: 78167-008 | Form: GEL
Manufacturer: Transformaciones Del Caribe, Sociedad Anonima
Category: otc | Type: HUMAN OTC DRUG LABEL
Date: 20201010

ACTIVE INGREDIENTS: ALCOHOL 70 mg/1 mL
INACTIVE INGREDIENTS: CARBOMER 934; PROPANEDIOL; WATER; TROLAMINE

Instant Hand Sanitizer Anti bacterial

Uses

* Helps eliminated bacterias on hand. This product is not a substitute of soap hand washing. Avoid contact with broken and damaged skin

Active Ingredient

Active Ingredient Purpose

- Ethyl Alcohol 70%...................................Antiseptic

Warnings

- For external use only
- When using this product avoid contact with eyes. In case of contact, flush with water for several minutes.
- Keep out of reach of children. If swallowed, get medical help, or contact a Poison Control Center right away.
- Stop use and ask Doctor: if skin irritation develops when using this product
- Flammable: Keep away from heat and flame. Highly flammable liquid and vapor/

Stop use and ask a doctor if

* Irritation develops while using this product

Keep out of reach of children. If swallowed, get medical help, or contact a Poison Control Center right away.

Directions

Directions: Place enough product in your palm to throughly cover your hands.

- Rubs hands together briskly until dry
- Children under 6 years of age should be supervised when using this product

Inactive Ingredients

water, carbomer, propylene glycol, triethanolamine

Questions?

QUESTIONS OR COMMENTS: Phone: (786) 871-6663

Uses

* Helps eliminated bacteria on hand. This product is not a substitute of soap hand washing. Avoid contact with broken and damaged skin